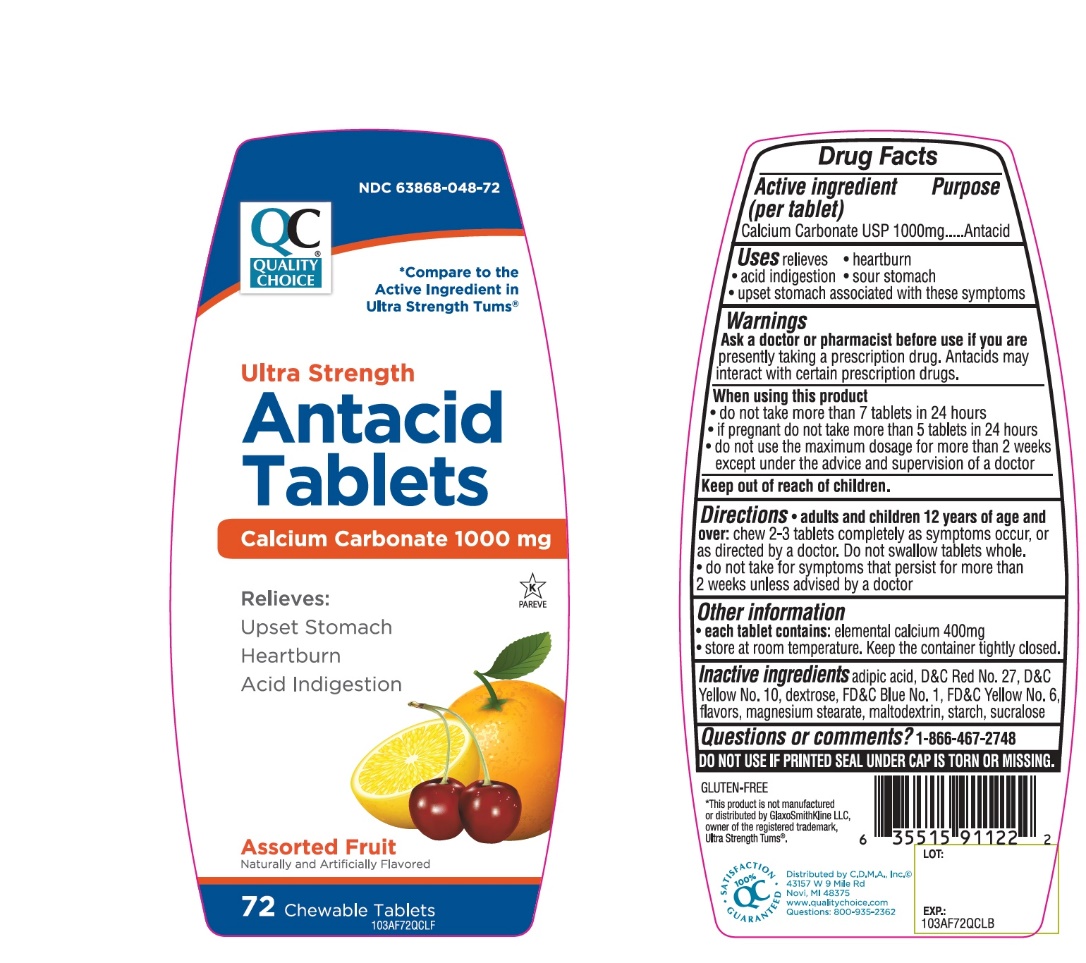 DRUG LABEL: Quality Choice Ultra Strength

NDC: 63868-048 | Form: TABLET, CHEWABLE
Manufacturer: CHAIN DRUG MARKETING ASSOCIATION
Category: otc | Type: HUMAN OTC DRUG LABEL
Date: 20251203

ACTIVE INGREDIENTS: CALCIUM CARBONATE 1000 mg/1 1
INACTIVE INGREDIENTS: ADIPIC ACID; FD&C BLUE NO. 1; DEXTROSE, UNSPECIFIED FORM; MAGNESIUM STEARATE; MALTODEXTRIN; D&C RED NO. 27; STARCH, CORN; SUCRALOSE; FD&C YELLOW NO. 6; D&C YELLOW NO. 10

Quality Choice Ultra Strength Antacid Calcium Carbonate 72 Chewable Tablets

Active ingredient (per tablet)

Calcium Carbonate USP 1000mg

Purpose

Antacid

Uses

relieves

- heartburn
- acid indigestion
- sour stomach
- upset stomach associated with these symptoms

Warnings

Ask a doctor or pharmacist before use if you arepresently taking a prescription drug. Antacids may interact with certain prescription drugs.

When using this product

- do not take more than 7 tablets in 24 hours
- do not use the maximum dosage for more than 2 weeks.

Directions

- Chew 2-3 tablets as symptoms occur, or as directed by a doctor.

Other information

- Store below 30°C (86°F)
- Keep the container tightly closed
- For calcium and magnesium content see Supplement Facts

SAFETY SEALED: DO NOT USE IF PRINTED SEAL UNDER CAP IS TORN OR MISSING

Inactive ingredients

adipic acid, FD&C Blue No. 1, dextrose, flavors, magnesium stearate, maltodextrin, D&C Red No. 27, starch, sucralose, FD&C Yellow No. 6, D&C Yellow No. 10.

Package/Label Principal Display Panel

NDC 63868-048-72

Compare to Tums®Ultra Strength active ingredient*

Ultra Strength

Antacid Tablets

Antacid Calcium Supplement

Calcium Carbonate 1000 mg

Relieves:

Upset Stomach

Heartburn

Acid Indigestion

Assorted Fruit

72 Chewable Tablets

K PAREVE

GLUTEN- FREE

QC SATISFACTION GURANTEED

©Distributed by C.D.M.A., Inc.,

43157 W. Nine Mile

www.qualitychoice.com

Questions: 248-449-9300

*This product is not manufactured or distributed by GlaxoSmithKline LLC, the distributor of Tums®.